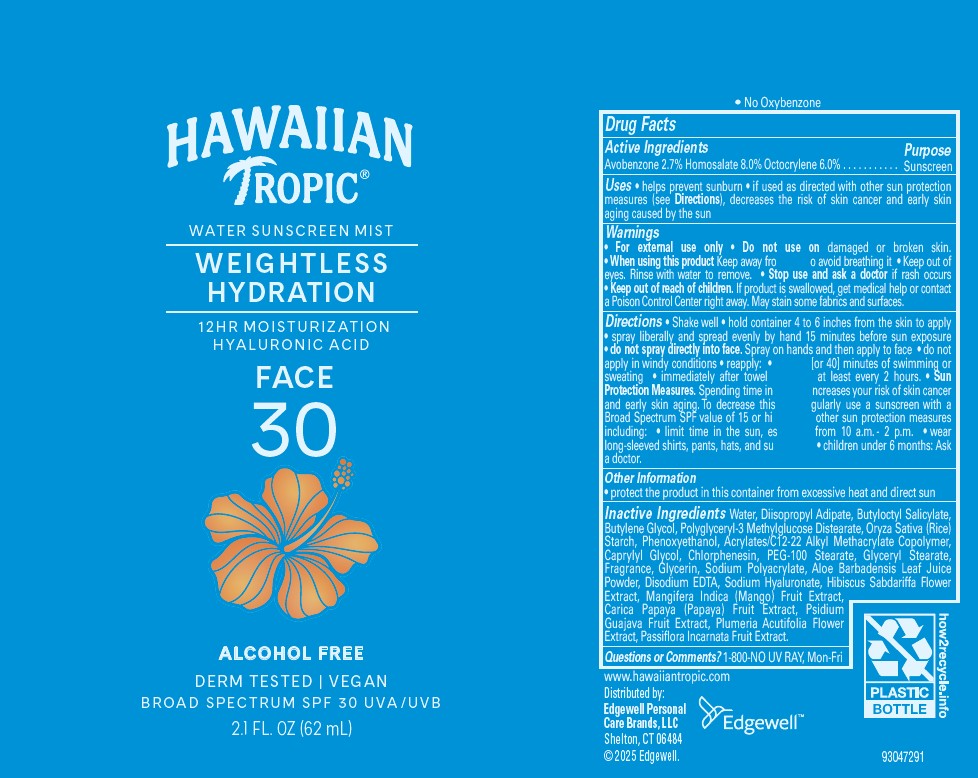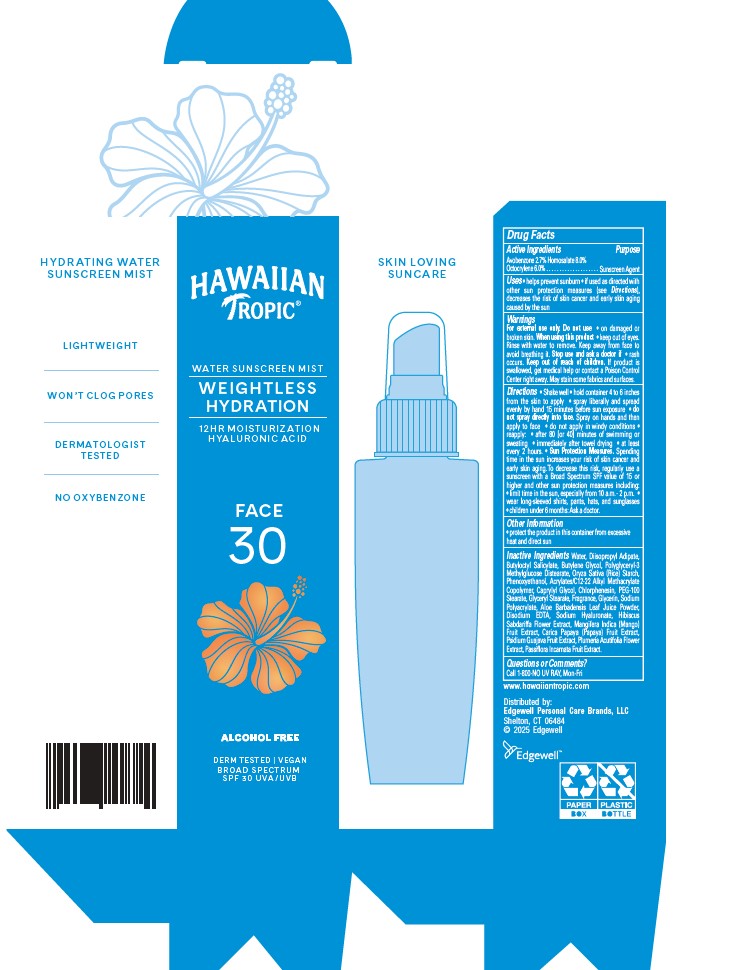 DRUG LABEL: HAWAIIAN TROPIC
NDC: 63354-712 | Form: SPRAY
Manufacturer: Edgewell Personal Care Brands LLC
Category: otc | Type: HUMAN OTC DRUG LABEL
Date: 20260106

ACTIVE INGREDIENTS: HOMOSALATE 8 g/100 g; OCTOCRYLENE 6 g/100 g; AVOBENZONE 2.7 g/100 g
INACTIVE INGREDIENTS: ALOE VERA LEAF; BUTYLOCTYL SALICYLATE; HYALURONATE SODIUM; SODIUM POLYACRYLATE (2500000 MW); CHLORPHENESIN; GLYCERIN; BUTYLENE GLYCOL; PASSIFLORA INCARNATA FRUIT; GLYCERYL MONOSTEARATE; PEG-100 STEARATE; GUAVA; EDETATE DISODIUM; HIBISCUS SABDARIFFA FLOWER; MANGO; PLUMERIA RUBRA FLOWER; WATER; DIISOPROPYL ADIPATE; POLYGLYCERYL-3 METHYLGLUCOSE DISTEARATE; STARCH, RICE; CAPRYLYL GLYCOL; PAPAYA; PHENOXYETHANOL

Active Ingredients

Avobenzone 2.7% Homosalate 8.0% Octocrylene 6.0%

Purpose

Sunscreen Agent

Uses

• helps prevent sunburn • if used as directed with other sun protection measures (see Directions), decreases the risk of skin cancer and early skin aging caused by the sun

Warnings

• For external use only

Do not use

on damaged or broken skin.

When using this product

Keep away from face to avoid breathing it • Keep out of eyes. Rinse with water to remove.

Stop use and ask a doctor

if rash occurs

Keep out of reach of children.

If product is swallowed, get medical help or contact a Poison Control Center right away. May stain some fabrics and surfaces.

Directions

• Shake well • Hold container 4 to 6 inches from the skin to apply. Don’t spray directly into face. Apply on hand then apply to face. Spray evenly and liberally on your skin. Apply 15 minutes before sun exposure. Reapply throughout the day • at least every 2 hours, • after 80 minutes of swimming orsweating • immediately after towel drying • Sun Protection Measures. Spending time in the sun increases your risk of skin cancer and early skin aging. To decrease this risk, regularly use a sunscreen with a broad spectrum SPF value of 15 or higher and other sun protection measures including: • limit time in the sun, especially from 10 a.m. - 2 p.m. • wear long-sleeved shirts, pants, hats, and sunglasses • children under 6 months: Ask a doctor

Inactive Ingredients

Water, Diisopropyl Adipate, Butyloctyl Salicylate, Butylene Glycol, Polyglyceryl-3 Methylglucose Distearate, Oryza Sativa (Rice) Starch, Phenoxyethanol, Acrylates/C12-22 Alkyl Methacrylate Copolymer, Caprylyl Glycol, Chlorphenesin, PEG-100 Stearate, Glyceryl Stearate, Fragrance, Glycerin, Sodium Polyacrylate, Aloe Barbadensis Leaf Juice Powder, Disodium EDTA, Sodium Hyaluronate, Hibiscus Sabdariffa Flower Extract, Mangifera Indica (Mango) Fruit Extract, Carica Papaya (Papaya) Fruit Extract, Psidium Guajava Fruit Extract, Plumeria Acutifolia Flower Extract, Passiflora Incarnata Fruit Extract.

Other Information

• protect this product from excessive heat and direct sun

Questions or Comments?

1-800-NO UV RAY, Mon-Fri

PACKAGE LABEL

HAWAIIAN TROPIC
WATER SUNSCREEN MIST
WEIGHTLESS
HYDRATION
12 HR MOISTURIZATION
HYALURONIC ACID

FACE
30
ALCOHOL FREE
DERM TESTED | VEGAN
BROAD SPECTRUM
SPF 30 UVA/UVB
2.1 FL. OZ (62 ml)

HAWAIIAN TROPIC
WATER SUNSCREEN MIST
WEIGHTLESS
HYDRATION
12 HR MOISTURIZATION
HYALURONIC ACID

FACE
30
ALCOHOL FREE
DERM TESTED | VEGAN
BROAD SPECTRUM SPF 30 UVA/UVB
2.1 FL. OZ (62 ml)